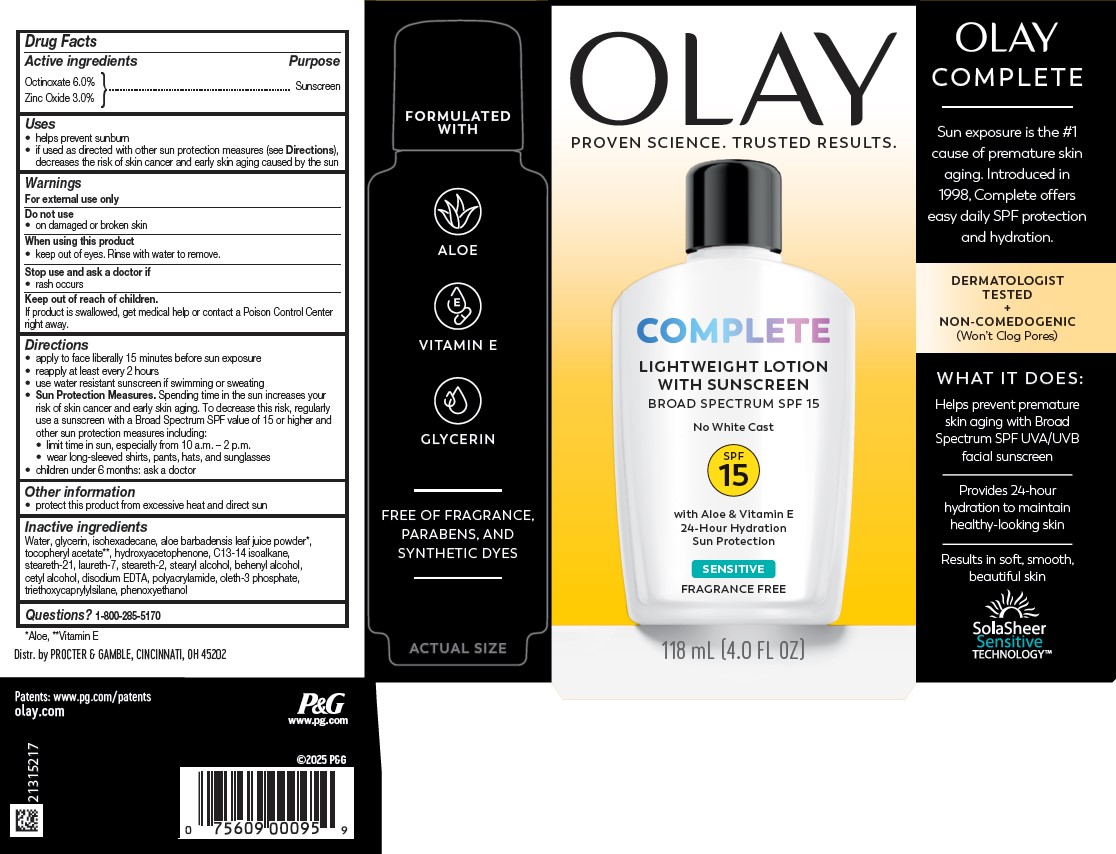 DRUG LABEL: Olay Complete Lightweight with Sunscreen Broad Spectrum SPF 15 Sensitive
NDC: 84126-162 | Form: LOTION
Manufacturer: The Procter & Gamble Manufacturing Company
Category: otc | Type: HUMAN OTC DRUG LABEL
Date: 20250819

ACTIVE INGREDIENTS: ZINC OXIDE 3 g/100 mL; OCTINOXATE 6 g/100 mL
INACTIVE INGREDIENTS: C13-14 ISOPARAFFIN; WATER; GLYCERIN; ISOHEXADECANE; .ALPHA.-TOCOPHEROL ACETATE; ALOE BARBADENSIS LEAF POWDER; STEARETH-21; STEARYL ALCOHOL; BEHENYL ALCOHOL; CETYL ALCOHOL; STEARETH-2; EDETATE DISODIUM; LAURETH-7; TRIETHOXYCAPRYLYLSILANE; OLETH-3 PHOSPHATE; HYDROXYACETOPHENONE; POLYACRYLAMIDE (1300000 MW); PHENOXYETHANOL

Olay Complete Lightweight Lotion with Sunscreen Broad Spectrum SPF 15 Sensitive

Drug Facts

ACTIVE INGREDIENT

Active ingredients | Purpose
Octinoxate 6% | Sunscreen
Zinc Oxide 3% | Sunscreen

Uses

- helps prevent sunburn
- if used as directed with other sun protection measures (see Directions), decreases the risk of skin cancer and early skin aging caused by the sun

Warnings

For external use only

Do not use

- on damaged or broken skin

When using this product

- keep out of eyes. Rinse with water to remove.

Stop use and ask a doctor if

- rash occurs

Keep out of reach of children. If product is swallowed, get medical help or contact a Poison Control Center right away.

Directions

- apply liberally 15 minutes before sun exposure
- reapply at least every 2 hours
- use water resistant sunscreen if swimming or sweating
- Sun Protection Measures. Spending time in the sun increases your risk of skin cancer and early skin aging. To decrease this risk, regularly use a sunscreen with a Broad Spectrum SPF value of 15 or higher and other sun protection measures including:
  - limit time in sun, especially from 10 a.m. – 2 p.m.
  - wear long-sleeved shirts, pants, hats, and sunglasses
- children under 6 months: ask a doctor

Other information

- protect this product from excessive heat and direct sun

Inactive ingredients

Water, glycerin, isohexadecane, aloe barbadensis leaf juice powder, tocopheryl acetate, hydroxyacetophenone, C13-14 isoalkane, steareth-21, laureth-7, steareth-2, stearyl alcohol, behenyl alcohol, cetyl alcohol, disodium EDTA, polyacrylamide, oleth-3 phosphate, triethoxycaprylylsilane, phenoxyethanol

Questions or comments?

Call 1-800-285-5170

Distr. by PROCTER & GAMBLE,
CINCINNATI, OH 45202

PRINCIPAL DISPLAY PANEL - 118 mL Bottle Carton

OLAY

COMPLETE

LIGHTWEIGHT LOTION

WITH SUNSCREEN

BROAD SPECTRUM SPF 15

SENSITIVE

FRAGRANCE FREE

118 mL (4.0 FL OZ)